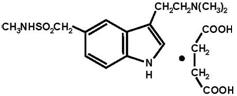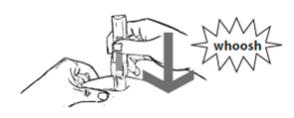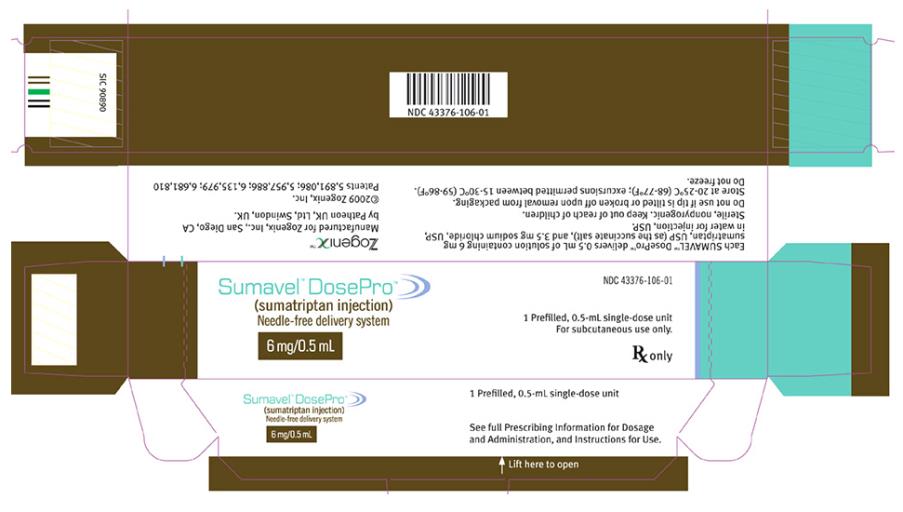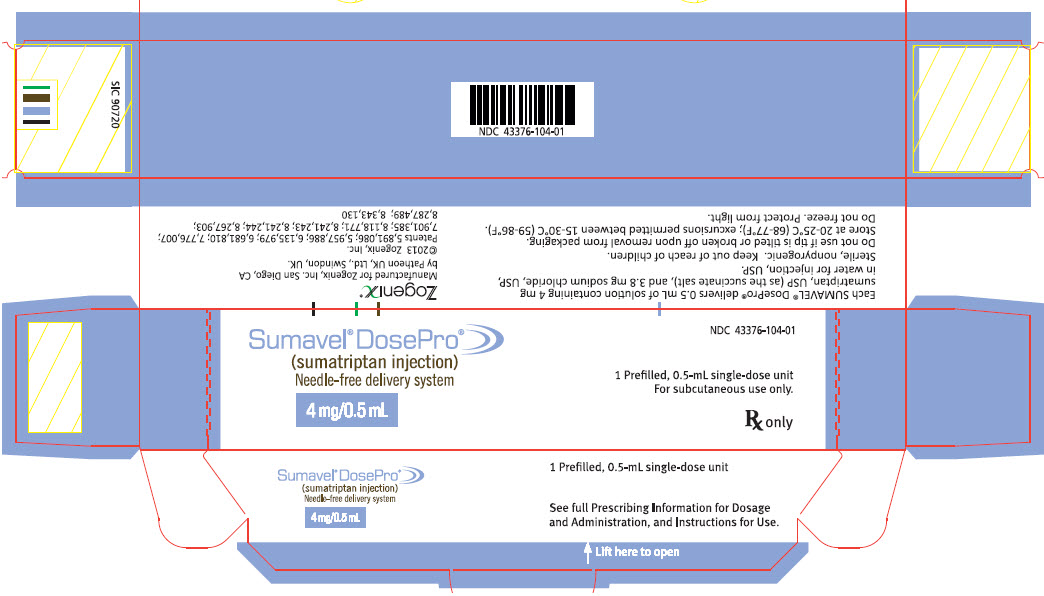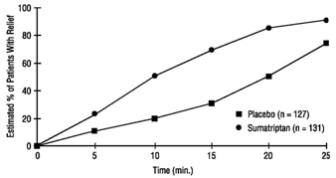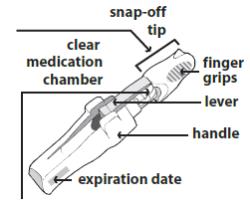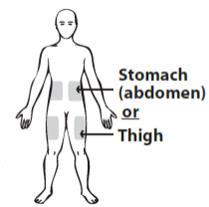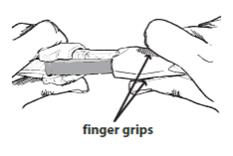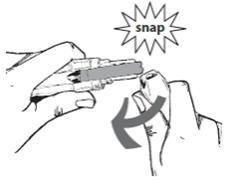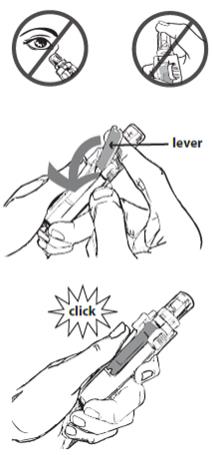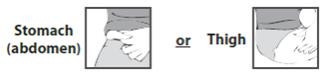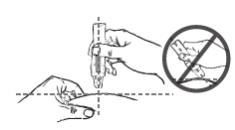 DRUG LABEL: Sumavel DosePro
NDC: 43376-106 | Form: INJECTION
Manufacturer: Zogenix, Inc.
Category: prescription | Type: HUMAN PRESCRIPTION DRUG LABEL
Date: 20140207

ACTIVE INGREDIENTS: SUMATRIPTAN SUCCINATE 6 mg/0.5 mL
INACTIVE INGREDIENTS: SODIUM CHLORIDE; WATER

HIGHLIGHTS OF PRESCRIBING INFORMATION

These highlights do not include all the information needed to use Sumavel DosePro safely and effectively. See full prescribing information for Sumavel DosePro.
Sumavel DosePro (sumatriptan injection), for subcutaneous use
Initial U.S. Approval: 1992

1 INDICATIONS AND USAGE

Sumavel® DosePro® is a serotonin (5-HT1B/1D) receptor agonist (triptan) indicated for:

- Acute treatment of migraine with or without aura in adults (1)
- Acute treatment of cluster headache in adults (1)

Limitations of Use:

- Use only if a clear diagnosis of migraine or cluster headache has been established. (1)
- Not indicated for the prevention of migraine attacks. (1)

2 DOSAGE AND ADMINISTRATION

- For subcutaneous use only. (2.1, 2.2)
- Acute treatment of migraine: 4 mg or 6 mg single dose. (2.1)
- Acute treatment of cluster headache: 6 mg single dose. (2.1)
- Maximum dose in a 24-hour period: 12 mg. Separate doses by at least 1 hour. (2.1)
- Administer dose only to the abdomen or thigh. (2.2)

DO NOT USE SUMAVEL DOSEPRO IF THE TIP OF THE DEVICE IS TITLED OR BROKEN OFF UPON REMOVAL FROM PACKAGING. (2.2)

3 DOSAGE FORMS AND STRENGTHS

- Sumavel DosePro: 4 mg or 6 mg prefilled, single-dose, needle-free subcutaneous delivery systems.

4 CONTRAINDICATIONS

- History of coronary artery disease or coronary vasospasm (4)
- Wolff-Parkinson-White syndrome or other cardiac accessory conduction pathway disorders (4)
- History of stroke, transient ischemic attack, or hemiplegic or basilar migraine (4)
- Peripheral vascular disease (4)
- Ischemic bowel disease (4)
- Uncontrolled hypertension (4)
- Recent (within 24 hours) use of another 5-HT1 agonist (e.g., another triptan) or of an ergotamine-containing medication (4)
- Current or recent (past 2 weeks) use of monoamine oxidase-A inhibitor
  (4)
- Hypersensitivity to Sumavel DosePro (angioedema and anaphylaxis seen) (4)

5 WARNINGS AND PRECAUTIONS

- Myocardial ischemia/infarction and Prinzmetal’s angina: Perform cardiac evaluation in patients with multiple cardiovascular risk factors. (5.1)
- Arrhythmias: Discontinue Sumavel DosePro if occurs. (5.2)
- Chest/throat/neck/jaw pain, tightness, pressure, or heaviness: Generally not associated with myocardial ischemia; evaluate for coronary artery disease in patients at high risk. (5.3)
- Cerebral hemorrhage, subarachnoid hemorrhage, or stroke: Discontinue Sumavel DosePro if occurs. (5.4)
- Gastrointestinal ischemia or infarction events, or peripheral vasospastic reactions: Discontinue Sumavel DosePro if occurs. (5.5)
- Medication overuse headache: Detoxification may be necessary. (5.6)
- Serotonin syndrome: Discontinue Sumavel DosePro if occurs. (5.7)
- Seizures: Use with caution in patients with epilepsy or a lowered seizure threshold. (5.10)

6 ADVERSE REACTIONS

Most common adverse reactions (≥5% and > placebo) were injection site reactions, tingling, dizziness/vertigo, warm/hot sensation, burning sensation, feeling of heaviness, pressure sensation, flushing, feeling of tightness, and numbness. (6.1)

To report SUSPECTED ADVERSE REACTIONS, contact Zogenix, Inc. at 1-866-ZOGENIX or FDA at 1-800-FDA-1088 or www.fda.gov/medwatch.

8 USE IN SPECIFIC POPULATIONS

- Pregnancy: Based on animal data, may cause fetal harm. (8.1)

FULL PRESCRIBING INFORMATION

1 INDICATIONS AND USAGE

Sumavel DosePro is indicated in adults for (1) the acute treatment of migraine, with or without aura, and (2) the acute treatment of cluster headache.
Limitations of Use:

- Use only if a clear diagnosis of migraine or cluster headache has been established.
- If a patient has no response to the first migraine attack treated with Sumavel DosePro, reconsider the diagnosis of migraine before Sumavel DosePro is administered to treat any subsequent attacks.
- Sumavel DosePro is not indicated for the prevention of migraine attacks.

2 DOSAGE AND ADMINISTRATION

2.1 Dosing Information

The maximum single recommended dose of Sumavel DosePro for the acute treatment of migraine or cluster headache is 6 mg given subcutaneously. For the treatment of migraine, if side effects are dose limiting, a lower dose (4 mg) may be used [see Clinical Studies (14.1)]. For the treatment of cluster headache, the efficacy of a lower dose has not been established.

The maximum cumulative injected dose that may be given in 24 hours is 12 mg, with doses of Sumavel DosePro separated by at least 1 hour. Sumavel DosePro may be given at least 1 hour following a dose of another sumatriptan product. A second dose should only be considered if some response to a first dose was observed.

2.2 Administration Using Sumavel® DosePro®

Sumavel DosePro is available for use as 4 mg or 6 mg needle-free delivery systems. It is intended to be given subcutaneously only. Sumavel DosePro is designed for patient self-administration to sites on the abdomen or the thigh with an adequate subcutaneous thickness to accommodate penetration of sumatriptan injection into the subcutaneous space. Administration should not be made within 2 inches of the naval. Sumavel DosePro is not to be administered to other areas of the body, including the arm.

Instruct patients on the proper use of Sumavel DosePro and direct them to use proper injection sites. Patients should be instructed not to use Sumavel DosePro if the tip of the device is tilted or broken off upon removal from packaging [see Patient counseling Information (17)].

Sumavel DosePro is for single use only. Discard after use.

3 DOSAGE FORMS AND STRENGTHS

Sumavel DosePro is a prefilled, single-dose, needle-free subcutaneous delivery system delivering 0.5 mL of sterile solution containing 4 mg or 6 mg sumatriptan (as the succinate salt).

4 CONTRAINDICATIONS

Sumavel DosePro is contraindicated in patients with:

- Ischemic coronary artery disease (CAD) (angina pectoris, history of myocardial infarction, or documented silent ischemia) or coronary artery vasospasm, including Prinzmetal’s angina [see Warnings and Precautions (5.1)]
- Wolff-Parkinson-White syndrome or arrhythmias associated with other cardiac accessory conduction pathway disorders [see Warnings and Precautions (5.2)]
- History of stroke or transient ischemic attack (TIA) because these patients are at a higher risk of stroke [see Warnings and Precautions (5.4)]
- History of hemiplegic or basilar migraine
- Peripheral vascular disease [see Warnings and Precautions (5.5)]
- Ischemic bowel disease [see Warnings and Precautions (5.5)]
- Uncontrolled hypertension [see Warnings and Precautions (5.8)]
- Recent (i.e., within 24 hours) use of ergotamine-containing medication, ergot-type medication (such as dihydroergotamine or methysergide), or another 5-hydroxytryptamine1 (5-HT1) agonist [see Drug Interactions (7.1, 7.3)]
- Concurrent administration of a monamine oxidase (MAO)-A inhibitor or recent (within 2 weeks) use of an MAO-A inhibitor [see Drug Interactions (7.2) and Clinical Pharmacology (12.3)]
- Hypersensitivity to Sumavel DosePro (angioedema and anaphylaxis seen) [see Warnings and Precautions (5.9) and Adverse Reactions (6)]

5 WARNINGS AND PRECAUTIONS

5.1 Myocardial Ischemia, Myocardial Infarction, and Prinzmetal’s Angina

Sumavel DosePro is contraindicated in patients with ischemic or vasospastic CAD. There have been rare reports of serious cardiac adverse reactions, including acute myocardial infarction, occurring within a few hours following administration of Sumavel DosePro. Some of these reactions occurred in patients without known CAD. Sumavel DosePro may cause coronary artery vasospasm (Prinzmetal’s angina), even in patients without a history of CAD.

Perform a cardiovascular evaluation in triptan-naive patients who have multiple cardiovascular risk factors (e.g., increased age, diabetes, hypertension, smoking, obesity, strong family history of CAD) prior to receiving Sumavel DosePro. If there is evidence of CAD or coronary artery vasospasm, Sumavel DosePro is contraindicated. For patients with multiple cardiovascular risk factors who have a negative cardiovascular evaluation, consider administering the first dose of Sumavel DosePro in a medically supervised setting and performing an electrocardiogram (ECG) immediately following Sumavel DosePro. For such patients, consider periodic cardiovascular evaluation in intermittent long-term users of Sumavel DosePro.

5.2 Arrhythmias

Life-threatening disturbances of cardiac rhythm, including ventricular tachycardia and ventricular fibrillation leading to death, have been reported within a few hours following the administration of 5-HT1 agonists. Discontinue Sumavel DosePro if these disturbances occur. Sumavel DosePro is contraindicated in patients with Wolff-Parkinson-White syndrome or arrhythmias associated with other cardiac accessory conduction pathway disorders.

5.3 Chest, Throat, Neck, and/or Jaw Pain/Tightness/Pressure

Sensations of tightness, pain, pressure, and heaviness in the precordium, throat, neck, and jaw commonly occur after treatment with Sumavel DosePro and are usually non-cardiac in origin. However, perform a cardiac evaluation if these patients are at high cardiac risk. The use of Sumavel DosePro is contraindicated in patients shown to have CAD and those with Prinzmetal’s variant angina.

5.4 Cerebrovascular Events

Cerebral hemorrhage, subarachnoid hemorrhage, and stroke have occurred in patients treated with 5-HT1 agonists, and some have resulted in fatalities. In a number of cases, it appears possible that the cerebrovascular events were primary, the 5-HT1 agonist having been administered in the incorrect belief that the symptoms experienced were a consequence of migraine when they were not. Also, patients with migraine may be at increased risk of certain cerebrovascular events (e.g., stroke, hemorrhage, TIA). Discontinue Sumavel DosePro if a cerebrovascular event occurs.

Before treating headaches in patients not previously diagnosed as migraineurs, and in migraineurs who present with atypical symptoms, exclude other potentially serious neurological conditions. Sumavel DosePro is contraindicated in patients with a history of stroke or TIA.

5.5 Other Vasospasm Reactions

Sumavel DosePro, may cause non-coronary vasospastic reactions, such as peripheral vascular ischemia, gastrointestinal vascular ischemia and infarction (presenting with abdominal pain and bloody diarrhea), splenic infarction, and Raynaud’s syndrome. In patients who experience symptoms or signs suggestive of non-coronary vasospasm reaction following the use of any 5-HT1 agonist, rule out a vasospastic reaction before receiving additional doses of Sumavel DosePro.

Reports of transient and permanent blindness and significant partial vision loss have been reported with the use of 5-HT1 agonists. Since visual disorders may be part of a migraine attack, a causal relationship between these events and the use of 5-HT1 agonists have not been clearly established.

5.6 Medication Overuse Headache

Overuse of acute migraine drugs (e.g., ergotamine, triptans, opioids, or combination of these drugs for 10 or more days per month) may lead to exacerbation of headache (medication overuse headache). Medication overuse headache may present as migraine-like daily headaches or as a marked increase in frequency of migraine attacks. Detoxification of patients, including withdrawal of the overused drugs, and treatment of withdrawal symptoms (which often includes a transient worsening of headache) may be necessary.

5.7 Serotonin Syndrome

Serotonin syndrome may occur with Sumavel DosePro, particularly during co-administration with selective serotonin reuptake inhibitors (SSRIs), serotonin norepinephrine reuptake inhibitors (SNRIs), tricyclic antidepressants (TCAs), and MAO inhibitors [see Drug Interactions (7.4)]. Serotonin syndrome symptoms may include mental status changes (e.g., agitation, hallucinations, coma), autonomic instability (e.g., tachycardia, labile blood pressure, hyperthermia), neuromuscular aberrations (e.g., hyperreflexia, incoordination), and/or gastrointestinal symptoms (e.g., nausea, vomiting, diarrhea). The onset of symptoms usually occurs within minutes to hours of receiving a new or a greater dose of a serotonergic medication. Discontinue Sumavel DosePro if serotonin syndrome is suspected.

5.8 Increase in Blood Pressure

Significant elevation in blood pressure, including hypertensive crisis with acute impairment of organ systems, has been reported on rare occasions in patients treated with 5-HT1 agonists, including patients without a history of hypertension. Monitor blood pressure in patients treated with Sumavel DosePro. Sumavel DosePro is contraindicated in patients with uncontrolled hypertension.

5.9 Anaphylactic/Anaphylactoid Reactions

There have been reports of anaphylaxis, anaphylactoid, and hypersensitivity reactions including angioedema in patients receiving Sumavel DosePro. Such reactions can be life threatening or fatal. In general, anaphylactic reactions to drugs are more likely to occur in individuals with a history of sensitivity to multiple allergens. Sumavel DosePro is contraindicated in patients with a history of hypersensitivity reaction to Sumavel DosePro.

5.10 Seizures

Seizures have been reported following administration of Sumavel DosePro. Some have occurred in patients with either a history of seizures or concurrent conditions predisposing to seizures. There are also reports in patients where no such predisposing factors are apparent. Sumavel DosePro should be used with caution in patients with a history of epilepsy or conditions associated with a lowered seizure threshold.

6 ADVERSE REACTIONS

The following adverse reactions are discussed in more detail in other sections of the labeling:

- Myocardial ischemia, myocardial infarction, and Prinzmetal’s angina [see Warnings and Precautions (5.1)]
- Arrhythmias [see Warnings and Precautions (5.2)]
- Chest, throat, neck, and/or jaw pain/tightness/pressure [see Warnings and Precautions (5.3)]
- Cerebrovascular events [see Warnings and Precautions (5.4)]
- Other vasospasm reactions [see Warnings and Precautions (5.5)]
- Medication overuse headache [see Warnings and Precautions (5.6)]
- Serotonin syndrome [see Warnings and Precautions (5.7)]
- Increase in blood pressure [see Warnings and Precautions (5.8)]
- Hypersensitivity reactions [see Contraindications (4) and Warnings and Precautions (5.9)]
- Seizures [see Warnings and Precautions (5.10)]

6.1 Clinical Trials Experience

Because clinical trials are conducted under widely varying conditions, adverse reaction rates observed in the clinical trials of a drug cannot be directly compared with rates in the clinical trials of another drug and may not reflect the rates observed in practice.

Migraine Headache: Table 1 lists adverse reactions that occurred in 2 US placebo-controlled clinical trials in migraine subjects [see Clinical Studies (14.1)] following either a single 6 mg dose of sumatriptan injection or placebo. Only reactions that occurred at a frequency of 2% or more in groups treated with sumatriptan injection 6 mg and that occurred at a frequency greater than the placebo group are included in Table 1.

Table 1. Adverse Reactions Reported by at Least 2% of Subjects and at a Greater Frequency Than Placebo in 2 Placebo-Controlled Migraine Clinical Trialsa
 | Percent of Subjects Reporting
Adverse Reaction | Sumatriptan Injection 6 mg Subcutaneous (n = 547) | Placebo (n = 370)
Atypical sensations Tingling Warm/hot sensation Burning sensation Feeling of heaviness Pressure sensation Feeling of tightness Numbness Feeling strange Tight feeling in head | 42 14 11 7 7 7 5 5 2 2 | 9 3 4 <1 1 2 <1 2 <1 <1
Cardiovascular Flushing | 7 | 2
Chest discomfort Tightness in chest Discomfort: nasal cavity/sinuses | 5 3 2 | 1 <1 <1
Injection site reactionb | 59 | 24
Miscellaneous Jaw discomfort | 2 | 0
Musculoskeletal Weakness Neck pain/stiffness Myalgia | 5 5 2 | <1 <1 <1
Neurological Dizziness/vertigo Drowsiness/sedation Headache | 12 3 2 | 4 2 <1
Skin Sweating | 2 | 1
a The sum of percentages cited is greater than 100% because subjects may have experienced more than 1 type of adverse reaction. Only reactions that occurred at a frequency of 2% or more in groups treated with sumatriptan injection and occurred at a frequency greater than that of the placebo group are included.
b Includes injection site pain, stinging/burning, swelling, erythema, bruising, bleeding.

The incidence of adverse reactions in controlled clinical trials was not affected by gender or age of the subjects. There were insufficient data to assess the impact of race on the incidence of adverse reactions.

Cluster Headache: In the controlled clinical trials assessing the efficacy of sumatriptan injection as a treatment for cluster headache [see Clinical Studies (14.2)], no new significant adverse reactions were detected that had not already been identified in trials of sumatriptan in subjects with migraine.

Overall, the frequency of adverse reactions reported in the trials of cluster headache was generally lower than in the migraine trials. Exceptions include reports of paresthesia (5% sumatriptan, 0% placebo), nausea and vomiting (4% sumatriptan, 0% placebo), and bronchospasm (1% sumatriptan, 0% placebo).

7 DRUG INTERACTIONS

7.1 Ergot-Containing Drugs

Ergot-containing drugs have been reported to cause prolonged vasospastic reactions. Because these effects may be additive, use of ergotamine-containing or ergot-type medications (like dihydroergotamine or methysergide) and Sumavel DosePro within 24 hours of each other is contraindicated.

7.2 Monoamine Oxidase-A Inhibitors

MAO-A inhibitors increase systemic exposure by 2-fold. Therefore, the use of Sumavel DosePro in patients receiving MAO-A inhibitors is contraindicated [see Clinical Pharmacology (12.3)].

7.3 Other 5-HT 1 Agonists

Because their vasospastic effects may be additive, co-administration of Sumavel DosePro and other 5-HT1 agonists (e.g., triptans) within 24 hours of each other is contraindicated.

7.4 Selective Serotonin Reuptake Inhibitors/Serotonin Norepinephrine Reuptake Inhibitors and Serotonin Syndrome

Cases of serotonin syndrome have been reported during co-administration of triptans and SSRIs, or SNRIs, SNRIs, TCAs, and MAO inhibitors [see Warnings and Precautions (5.7)].

8 USE IN SPECIFIC POPULATIONS

8.1 Pregnancy

Pregnancy Category C: There are no adequate and well-controlled trials of sumatriptan injection in pregnant women. Sumavel DosePro should be used during pregnancy only if the potential benefit justifies the potential risk to the fetus.

When sumatriptan was administered intravenously to pregnant rabbits daily throughout the period of organogenesis, embryolethality was observed at doses at or close to those producing maternal toxicity. These doses were less than the maximum recommended human dose (MRHD) of 12 mg/day on a mg/m^2 basis. Oral administration of sumatriptan to rabbits during organogenesis was associated with increased incidences of fetal vascular and skeletal abnormalities. The highest no-effect dose for these effects was 15 mg/kg/day. The intravenous administration of sumatriptan to pregnant rats throughout organogenesis at doses that are approximately 10 times the MRHD on a mg/m^2 basis, did not produce evidence of embryolethality. The subcutaneous administration to pregnant rats prior to and throughout pregnancy did not produce evidence of embryolethality or teratogenicity.

8.3 Nursing Mothers

It is not known whether sumatriptan is excreted in human breast milk following subcutaneous administration. Because many drugs are excreted in human milk, and because of the potential for serious adverse reactions in nursing infants from Sumavel DosePro, a decision should be made whether to discontinue nursing or to discontinue the drug, taking into account the importance of the drug to the mother.

8.4 Pediatric Use

Safety and effectiveness of sumatriptan injection in pediatric patients under 18 years of age have not been established; therefore, sumatriptan injection is not recommended for use in patients under 18 years of age.

Two controlled clinical trials evaluated sumatriptan nasal spray (5 to 20 mg) in 1,248 adolescent migraineurs aged 12 to 17 years who treated a single attack. The trials did not establish the efficacy of sumatriptan nasal spray compared with placebo in the treatment of migraine in adolescents. Adverse reactions observed in these clinical trials were similar in nature to those reported in clinical trials in adults.

Five controlled clinical trials (2 single-attack trials, 3 multiple-attack trials) evaluating oral sumatriptan (25 to 100 mg) in pediatric subjects aged 12 to 17 years enrolled a total of 701 adolescent migraineurs. These trials did not establish the efficacy of oral sumatriptan compared with placebo in the treatment of migraine in adolescents. Adverse reactions observed in these clinical trials were similar in nature to those reported in clinical trials in adults. The frequency of all adverse reactions in these subjects appeared to be both dose- and age-dependent, with younger subjects reporting reactions more commonly than older adolescents.

Postmarketing experience documents that serious adverse reactions have occurred in the pediatric population after use of subcutaneous, oral, and/or intranasal sumatriptan. These reports include reactions similar in nature to those reported rarely in adults, including stroke, visual loss, and death. A myocardial infarction has been reported in a 14-year-old male following the use of oral sumatriptan; clinical signs occurred within 1 day of drug administration. Since clinical data to determine the frequency of serious adverse reactions in pediatric patients who might receive subcutaneous, oral, or intranasal sumatriptan are not presently available, the use of sumatriptan in patients under 18 years of age is not recommended.

8.5 Geriatric Use

Clinical trials of sumatriptan injection did not include sufficient numbers of subjects aged 65 and over to determine whether they respond differently from younger subjects. Other reported clinical experience has not identified differences in responses between the elderly and younger subjects. In general, dose selection for an elderly patient should be cautious, usually starting at the low end of the dosing range, reflecting the greater frequency of decreased hepatic, renal, or cardiac function and of concomitant disease or other drug therapy.

A cardiovascular evaluation is recommended for geriatric patients who have other cardiovascular risk factors (e.g., diabetes, hypertension, smoking, obesity, strong family history of CAD) prior to receiving Sumavel DosePro [see Warnings and Precautions (5.1)].

8.6 Hepatic Impairment

The effect of severe hepatic impairment on Sumavel DosePro metabolism has not been evaluated. Sumavel DosePro is not recommended for use in patients with severe hepatic impairment [see Clinical Pharmacology (12.3)].

10 OVERDOSAGE

The elimination half-life of sumatriptan is about 2 hours [see Clinical Pharmacology (12.3)], and therefore monitoring of patients after overdose with subcutaneous sumatriptan should continue for at least 10 hours or while symptoms or signs persist. It is unknown what effect hemodialysis or peritoneal dialysis has on the serum concentrations of sumatriptan.

11 DESCRIPTION

Sumavel DosePro contains sumatriptan succinate, a selective 5-HT1B/1D receptor agonist. Sumatriptan succinate is chemically designated as 3-[2-(dimethylamino)ethyl]-N-methyl-indole-5-methanesulfonamide succinate (1:1), and it has the following structure:

The empirical formula is C14H21N3O2S•C4H6O4, representing a molecular weight of 413.5. Sumatriptan succinate is a white to off-white powder that is readily soluble in water and in saline.

Sumatriptan solution is a clear, colorless to pale yellow, sterile, nonpyrogenic solution for subcutaneous delivery. Each 0.5 mL of Sumavel DosePro 8 mg/mL solution contains 4 mg of sumatriptan (base) as the succinate salt and 3.8 mg of sodium chloride, USP in Water for Injection, USP. Each 0.5 mL of Sumavel DosePro 12 mg/mL solution contains 6 mg of sumatriptan (base) as the succinate salt and 3.5 mg of sodium chloride, USP, in water for injection, USP. The pH range of both solutions is approximately 4.2 to 5.3. The osmolality of both solutions is 291 mOsmol.

Sumavel DosePro is a pre-filled, single-use, disposable, needle-free subcutaneous delivery system delivering sterile sumatriptan injection. Sumavel DosePro consists of the following components: a gray plastic handle and snap-off tip, a lavender (4 mg) or green (6 mg) lever, and a glass medication chamber that is pre-filled with 4 mg or 6 mg per 0.5 mL sumatriptan injection. Utilizing pressure from a compressed nitrogen gas source in the handle, Sumavel DosePro delivers the medication by pushing it through a small, precise hole in the glass medication chamber. The resulting stream of medication is propelled through the skin and is delivered subcutaneously without a needle, following a biphasic pressure profile.

12 CLINICAL PHARMACOLOGY

12.1 Mechanism of Action

Sumatriptan is the active component of Sumavel DosePro. Sumatriptan binds with high affinity to human cloned 5-HT1B/1D receptors. Sumatriptan presumably exerts its therapeutic effects in the treatment of migraine headache by binding to 5-HT1B/1D receptors located on intracranial blood vessels and sensory nerves of the trigeminal system.

Current theories proposed to explain the etiology of migraine headache suggest that symptoms are due to local cranial vasodilatation and/or to the release of sensory neuropeptides (including substance P and calcitonin gene-related peptide) through nerve endings in the trigeminal system. The therapeutic activity of sumatriptan for the treatment of migraine and cluster headaches is thought to be due to the agonist effects at the 5-HT1B/1D receptors on intracranial blood vessels (including the arterio-venous anastomoses) and sensory nerves of the trigeminal system, which result in cranial vessel constriction and inhibition of pro-inflammatory neuropeptide release.

12.2 Pharmacodynamics

Blood Pressure: Significant elevation in blood pressure, including hypertensive crisis, has been reported in patients with and without a history of hypertension [see Warnings and Precautions (5.8)].

Peripheral (Small) Arteries: In healthy volunteers (N = 18), a trial evaluating the effects of sumatriptan on peripheral (small vessel) arterial reactivity failed to detect a clinically significant increase in peripheral resistance.

Heart Rate: Transient increases in blood pressure observed in some subjects in clinical trials carried out during sumatriptan’s development as a treatment for migraine were not accompanied by any clinically significant changes in heart rate.

12.3 Pharmacokinetics

Absorption and Bioavailability: Sumavel DosePro is bioequivalent to sumatriptan needle-based injection via autoinjector at the thigh and abdomen administration sites. A sub-optimal dose may be delivered when administered to the arm and therefore, the arm is not recommended as a site of administration.

Pharmacokinetic parameters following a 6 mg subcutaneous dose of Sumavel DosePro into the thigh were determined in 32 subjects (males and females). The maximum serum concentration (Cmax) (mean ± standard deviation) was 71.9 ± 14.4 ng/mL; the time to peak concentration (Tmax) was 12 minutes after dosing (range, 4 to 20 minutes); and the terminal half-life was 103 ± 22 minutes.

Pharmacokinetic parameters following a 6 mg subcutaneous dose of Sumavel DosePro into the abdomen were determined in 35 subjects (males and females). The maximum serum concentration (Cmax) (mean ± standard deviation) was 78.6 ± 17.3 ng/mL; the time to peak concentration (Tmax) was 12 minutes after dosing (range, 6 to 20 minutes); and the terminal half-life was 102 ± 12 minutes.

Distribution: The bioavailability of sumatriptan via subcutaneous site injection to 18 healthy male subjects was 97% ± 16% of that obtained following intravenous injection. Protein binding, determined by equilibrium dialysis over the concentration range of 10 to 1,000 ng/mL, is low, approximately 14% to 21%. The effect of sumatriptan on the protein binding of other drugs has not been evaluated.

Metabolism: In vitro studies with human microsomes suggest that sumatriptan is metabolized by MAO, predominantly the A isoenzyme. Most of a radiolabeled dose of sumatriptan excreted in the urine is the major metabolite indole acetic acid (IAA) or the IAA glucuronide, both of which are inactive.

Elimination: After a single 6 mg subcutaneous dose, 22% ± 4% was excreted in the urine as unchanged sumatriptan and 38% ± 7% as the IAA metabolite.

Special Populations: Age: The pharmacokinetics of sumatriptan in the elderly (mean age: 72 years, 2 males and 4 females) and in subjects with migraine (mean age: 38 years, 25 males and 155 females) were similar to that in healthy male subjects (mean age: 30 years).

Renal Impairment: The effect of renal impairment on the pharmacokinetics of sumatriptan has not been examined.

Hepatic Impairment: The effect of mild to moderate hepatic disease on the pharmacokinetics of subcutaneously administered sumatriptan has been evaluated. There were no significant differences in the pharmacokinetics of subcutaneously administered sumatriptan in moderately hepatically impaired subjects compared with healthy controls. The pharmacokinetics of subcutaneously administered sumatriptan in patients with severe hepatic impairment has not been studied. The use of Sumavel DosePro in this population is not recommended [see Use in Specific Populations (8.6)].

Race: The systemic clearance and Cmax of sumatriptan were similar in Black (n = 34) and Caucasian (n = 38) healthy male subjects.

Drug Interaction Studies: Monoamine Oxidase-A Inhibitors: In a trial of 14 healthy females, pretreatment with an MAO-A inhibitor decreased the clearance of sumatriptan, resulting in a 2-fold increase in the area under the sumatriptan plasma concentration-time curve (AUC), corresponding to a 40% increase in elimination half-life.

13 NONCLINICAL TOXICOLOGY

13.1 Carcinogenesis, Mutagenesis, Impairment of Fertility

Carcinogenesis: In carcinogenicity studies, rats and mice were given sumatriptan by oral gavage. Mice were dosed for 78 weeks and rats were dosed for 104 weeks. Average exposures achieved in mice receiving the highest dose were approximately 110 times the exposure attained in humans after the maximum recommended single dose of 6 mg. The highest dose to rats was approximately 260 times the maximum single dose of 6 mg on a mg/m^2 basis. There was no evidence of an increase in tumors in either species related to sumatriptan administration.

Mutagenesis: Sumatriptan was not mutagenic in the presence or absence of metabolic activation when tested in 2 gene mutation assays (the Ames test and the in vitro mammalian Chinese hamster V79/HGPRT assay). It was not clastogenic in 2 cytogenetics assays (the in vitro human lymphocyte assay and the in vivo rat micronucleus assay).

Impairment of Fertility: A fertility study (Segment I) by the subcutaneous route, during which male and female rats were dosed daily with sumatriptan prior to and throughout the mating period, has shown no evidence of impaired fertility at doses equivalent to approximately 100 times the maximum recommended single human dose of 6 mg on a mg/m^2 basis. However, following oral administration, a treatment-related decrease in fertility, secondary to a decrease in mating, was seen for rats treated with 50 and 500 mg/kg/day. The no-effect dose for this finding was approximately 8 times the maximum recommended single human dose of 6 mg on a mg/m^2 basis. It is not clear whether the problem is associated with the treatment of males or females or both.

13.2 Animal Toxicology and/or Pharmacology

Corneal Opacities: Dogs receiving oral sumatriptan developed corneal opacities and defects in the corneal epithelium. Corneal opacities were seen at the lowest dosage tested, 2 mg/kg/day, and were present after 1 month of treatment. Defects in the corneal epithelium were noted in a 60-week study. Earlier examinations for these toxicities were not conducted and no-effect doses were not established; however, the relative exposure at the lowest dose tested was approximately 5 times the human exposure after a 100 mg oral dose or 3 times the human exposure after a 6 mg subcutaneous dose.

Melanin Binding: In rats with a single subcutaneous dose (0.5 mg/kg) of radiolabeled sumatriptan, the elimination half-life of radioactivity from the eye was 15 days, suggesting that sumatriptan and its metabolites bind to the melanin of the eye. The clinical significance of this binding is unknown.

14 CLINICAL STUDIES

14.1 Migraine

In controlled clinical trials enrolling more than 1,000 subjects during migraine attacks who were experiencing moderate or severe pain and 1 or more of the symptoms enumerated in Table 3, onset of relief began as early as 10 minutes following a 6 mg sumatriptan injection. Lower doses of sumatriptan injection may also prove effective, although the proportion of subjects obtaining adequate relief was decreased and the latency to that relief is greater with lower doses. In one well-controlled study, 6 different doses of sumatriptan injection (n = 30 each group) were compared with placebo (n = 62), in a single-attack, parallel-group design, the dose response relationship was found to be as shown in Table 2.

Table 2. Proportion of Subjects with Migraine Relief and Incidence of Adverse Events by Time and by Sumatriptan Dose
Dose of Sumatriptan Injection | Percent Subjects with Reliefa |  |  |  | Adverse Events Incidence (%)
 | at 10 Minutes | at 30 Minutes | at 1 Hour | at 2 Hours
Placebo | 5 | 15 | 24 | 21 | 55
1 mg | 10 | 40 | 43 | 40 | 63
2 mg | 7 | 23 | 57 | 43 | 63
3 mg | 17 | 47 | 57 | 60 | 77
4 mg | 13 | 37 | 50 | 57 | 80
6 mg | 10 | 63 | 73 | 70 | 83
8 mg | 23 | 57 | 80 | 83 | 93
a Relief is defined as the reduction of moderate or severe pain to no pain or mild pain after dosing without use of rescue medication.

In 2 randomized, placebo-controlled clinical trials of sumatriptan injection 6 mg in 1,104 subjects with moderate or severe migraine pain, the onset of relief was less than 10 minutes. Headache relief, as defined by a reduction in pain from severe or moderately severe to mild or no headache, was achieved in 70% of the subjects within 1 hour of a single 6 mg subcutaneous dose of sumatriptan injection. Approximately 82% and 65% of subjects treated with sumatriptan 6 mg had headache relief and were pain free within 2 hours, respectively.

Table 3 shows the 1- and 2-hour efficacy results for sumatriptan injection 6 mg.

Table 3. Proportion of Subjects with Pain Relief and Relief of Migraine Symptoms After 1 and 2 Hours of Treatment
1-Hour Data | Study 1 |  | Study 2
 | Placebo (n = 190) | Sumatriptan Injection 6 mg (n = 384) | Placebo (n = 180) | Sumatriptan Injection 6 mg (n = 350)
Subjects with pain relief (grade 0/1) | 18% | 70%a | 26% | 70%a
Subjects with no pain | 5% | 48%a | 13% | 49%a
Subjects without nausea | 48% | 73%a | 50% | 73%a
Subjects without photophobia | 23% | 56%a | 25% | 58%a
Subjects with little or no clinical disabilityb | 34% | 76%a | 34% | 76%a
2-Hour Datac
Subjects with pain relief (grade 0/1) | 31% | 81%a | 39% | 82%a
Subjects with no pain | 11% | 63%a | 19% | 65%a
Subjects without nausea | 56% | 82%a | 63% | 81%a
Subjects without photophobia | 31% | 72%a | 35% | 71%a
Subjects with little or no clinical disabilityb | 42% | 85%a | 49% | 84%a
a P<0.05 versus placebo.
b A successful outcome in terms of clinical disability was defined prospectively as ability to work mildly impaired or ability to work and function normally.
c Includes patients who may have received an additional injection of the assigned treatment (placebo or sumatriptan 6 mg) 1 hour after the initial injection.

Subcutaneous sumatriptan also relieved photophobia, phonophobia (sound sensitivity), nausea, and vomiting associated with migraine attacks. The efficacy of sumatriptan injection was unaffected by whether or not the migraine was associated with aura, duration of attack, gender or age of the subject, or concomitant use of common migraine prophylactic drugs (e.g., beta-blockers).

14.2 Cluster Headache

The efficacy of sumatriptan injection in the acute treatment of cluster headache was demonstrated in 2 randomized, double-blind, placebo-controlled, 2-period crossover trials. Subjects aged 21 to 65 years were enrolled and were instructed to treat a moderate to very severe headache within 10 minutes of onset. Headache relief was defined as a reduction in headache severity to mild or no pain. In both trials, the proportion of individuals gaining relief at 10 or 15 minutes was significantly greater among subjects receiving 6 mg of sumatriptan injection compared with those who received placebo (see Table 4).

Table 4. Proportion of Subjects with Cluster Headache Relief by Time
 | Study 1 |  | Study 2
 | Placebo (n = 39) | Sumatriptan Injection 6 mg (n = 39) | Placebo (n = 88) | Sumatriptan Injection 6 mg (n = 92)
Subjects with pain relief (no/mild)
5 Minutes post-injection | 8% | 21% | 7% | 23%a
10 Minutes post-injection | 10% | 49%a | 25% | 49%a
15 Minutes post-injection | 26% | 74%a | 35% | 75%a
a P<0.05.
(n = Number of headaches treated.)

An estimate of the cumulative probability of a subject with a cluster headache obtaining relief after being treated with either sumatriptan or placebo is presented in Figure 1.

Figure 1. Time to Relief of Cluster Headache from Time of Injectiona

a The figure uses Kaplan-Meier (product limit) Survivorship Plot. Subjects taking rescue medication were censored at 15 minutes.

The plot was constructed with data from subjects who either experienced relief or did not require (request) rescue medication within a period of 2 hours following treatment. As a consequence, the data in the plot are derived from only a subset of the 258 headaches treated (rescue medication was required in 52 of the 127 placebo-treated headaches and 18 of the 131 headaches treated with sumatriptan injection).

Other data suggest that treatment with sumatriptan injection is not associated with an increase in early recurrence of headache and has little effect on the incidence of later-occurring headaches (i.e., those occurring after 2, but before 18 or 24 hours).

16 HOW SUPPLIED/STORAGE AND HANDLING

Each Sumavel DosePro needle-free delivery system contains sumatriptan (base) in 0.5 mL, in a sterile, nonpyrogenic solution and is supplied as follows:

- Sumavel DosePro, 4 mg in a package of six prefilled, single-dose units (NDC 43376-104-06).
- Sumavel DosePro, 6 mg in a package of six prefilled, single-dose units (NDC 43376-106-06).

Store at 20 oC to 25 oC (68 oF to 77 oF), with excursions permitted between 15 oC to 30 oC (59 oF to 86 oF). Do not freeze. Protect from light.

17 PATIENT COUNSELING INFORMATION

See FDA-approved patient labeling.

Risk of Myocardial Ischemia and/or Infarction, Prinzmetal’s Angina, Other Vasospasm-Related Events, Arrhythmias and Cerebrovascular Events
Inform patients that Sumavel DosePro may cause serious cardiovascular side effects such as myocardial infarction or stroke. Although serious cardiovascular events can occur without warning symptoms, patients should be alert for the signs and symptoms of chest pain, shortness of breath, irregular heartbeat, significant rise in blood pressure, weakness, and slurring of speech and should ask for medical advice when observing any indicative sign or symptoms. Patients should be apprised of the importance of this follow-up [see Warnings and Precautions (5.1, 5.2, 5.4, 5.5, 5.8)].

Anaphylactic/Anaphylactoid Reactions
Inform patients that anaphylactic/anaphylactoid reactions have occurred in patients receiving Sumavel DosePro. Such reactions can be life threatening or fatal. In general, anaphylactic reactions to drugs are more likely to occur in individuals with a history of sensitivity to multiple allergens [see Warnings and Precautions (5.9)].

Serotonin Syndrome
Patients should be cautioned about the risk of serotonin syndrome with the use of Sumavel DosePro or other triptans, particularly during combined use with SSRIs, SNRIs, TCAs, and MAO inhibitors [see Warnings and Precautions (5.7) and Drug Interactions (7.4)].

Medication Overuse Headache
Inform patients that use of acute migraine drugs for 10 or more days per month may lead to an exacerbation of headache and encourage patients to record headache frequency and drug use (e.g., by keeping a headache diary) [see Warnings and Precautions (5.6)].

Pregnancy
Inform patients that Sumavel DosePro should not be used during pregnancy unless the potential benefit justifies the potential risk to the fetus [see Use in Specific Populations (8.1)].

Nursing Mothers
Advise patients to notify their healthcare provider if they are breastfeeding or plan to breastfeed [see Use in Specific Populations (8.3)].

Ability to Perform Complex Tasks
Since migraines or treatment with Sumavel DosePro may cause somnolence and dizziness, instruct patients to evaluate their ability to perform complex tasks during migraine attacks and after administration of Sumavel DosePro.

How to Use Sumavel DosePro
Importance of Training
Patients who are to self-administer Sumavel DosePro in medically unsupervised situations should receive instruction on the proper use of Sumavel DosePro from the physician or healthcare professional prior to administering for the first time.
Patients should be made aware that a loud burst of air will be heard and a sensation felt at the time the dose is delivered via Sumavel DosePro. Patients should be advised not to use a device if the tip of the device is tilted or broken off upon removal from packaging.

Choosing Administration Sites
Sumavel DosePro delivers the medication to the subcutaneous space in a manner similar to a subcutaneous injection. Since delivery is to be given subcutaneously, patients should be instructed to use administration sites on the abdomen or the thigh with adequate subcutaneous thickness to accommodate penetration of the drug into the subcutaneous space. Administration should not be made within 2 inches of the navel. Instruct patients not to administer Sumavel DosePro to the arms or other areas of the body. Inform patients that Sumavel DosePro is for subcutaneous use only and is not designed for intramuscular or intravenous use.

Patient Information
Sumavel® DosePro® (SUE-muh-vell DOSE-pro)
(sumatriptan injection)
Needle-free Delivery System

Read this Patient Information before you start using Sumavel DosePro and each time you get a refill. There may be new information. This information does not take the place of talking with your healthcare provider about your medical condition or treatment.

What is the most important information I should know about Sumavel DosePro? Sumavel DosePro can cause serious side effects, including:
Heart attack and other heart problems. Heart problems may lead to death.

Stop taking Sumavel DosePro and get emergency medical help right away if you have any of the following symptoms of a heart attack:

- discomfort in the center of your chest that lasts for more than a few minutes, or that goes away and comes back
- severe tightness, pain, pressure, or heaviness in your chest, throat, neck, or jaw
- pain or discomfort in your arms, back, neck, jaw, or stomach
- shortness of breath with or without chest discomfort
- breaking out in a cold sweat
- nausea or vomiting
- feeling lightheaded

Sumavel DosePro is not for people with risk factors for heart disease unless a heart exam is done and shows no problem. You have a higher risk for heart disease if you:

- have high blood pressure
- have high cholesterol levels
- smoke
- are overweight
- have diabetes
- have a family history of heart disease

What is Sumavel DosePro?

Sumavel DosePro is a prescription medicine used to treat acute migraine headaches with or without aura and acute cluster headaches in adults who have been diagnosed with migraine or cluster headaches.

Sumavel DosePro is not used to treat other types of headaches such as hemiplegic (that make you unable to move on one side of your body) or basilar (rare form of migraine with aura) migraines.

Sumavel DosePro is not used to prevent or decrease the number of migraine or cluster headaches you have.

It is not known if Sumavel DosePro is safe and effective in children under 18 years of age.

Who should not take Sumavel DosePro?

Do not take Sumavel DosePro if you have:

- heart problems or a history of heart problems
- narrowing of blood vessels to your legs, arms, stomach, or kidney (peripheral vascular disease)
- uncontrolled high blood pressure
- hemiplegic migraines or basilar migraines. If you are not sure if you have these types of migraines, ask your healthcare provider.
- had a stroke, transient ischemic attacks (TIAs), or problems with your blood circulation
- taken any of the following medicines in the last 24 hours:
  • almotriptan (AXERT®)
  • eletriptan (RELPAX®)
  • frovatriptan (FROVA®)
  • naratriptan (AMERGE®)
  • rizatriptan (MAXALT®, MAXALT-MLT®)
  • ergotamines (CAFERGOT®, ERGOMAR®, MIGERGOT®)
  • dihydroergotamine (D.H.E. 45®, MIGRANAL®)
  Ask your healthcare provider if you are not sure if your medicine is listed above.
- are allergic to sumatriptan or any of the ingredients in Sumavel DosePro. See the end of this leaflet for a complete list of ingredients in Sumavel DosePro.

What should I tell my healthcare provider before taking Sumavel DosePro?

Before you take Sumavel DosePro, tell your healthcare provider about all of your medical conditions, including if you:

- have high blood pressure
- have high cholesterol
- have diabetes
- smoke
- are overweight
- have heart problems or family history of heart problems or stroke
- have liver problems
- have had epilepsy or seizures
- are not using effective birth control
- become pregnant while taking Sumavel DosePro
- are breastfeeding or plan to breastfeed. Sumavel DosePro passes into your breast milk and may harm your baby. Talk with your healthcare provider about the best way to feed your baby if you take Sumavel DosePro.

Tell your healthcare provider about all the medicines you take, including prescription and over-the-counter medicines, vitamins, and herbal supplements.

Using Sumavel DosePro with certain other medicines can affect each other, causing serious side effects.

Especially tell your healthcare provider if you take anti-depressant medicines called:

- selective serotonin reuptake inhibitors (SSRIs)
- serotonin norepinephrine reuptake inhibitors (SNRIs)
- tricyclic antidepressants (TCAs)
- monoamine oxidase inhibitors (MAOIs)

Ask your healthcare provider or pharmacist for a list of these medicines if you are not sure.

Know the medicines you take. Keep a list of them to show your healthcare provider or pharmacist when you get a new medicine.

How should I take Sumavel DosePro?

- See the Instructions for Use at the end of this leaflet for complete information on how to use Sumavel DosePro.
- Certain people should take their first dose of Sumavel DosePro in their healthcare provider’s office or in another medical setting. Ask your healthcare provider if you should take your first dose in a medical setting.
- Use Sumavel DosePro exactly as your healthcare provider tells you to use it.
- Before you try to inject Sumavel DosePro yourself, a healthcare provider should teach you how to use the Sumavel DosePro Needle-free Delivery System.
- Your healthcare provider may change your dose. Do not change your dose without first talking to your healthcare provider.
- You should use Sumavel DosePro as soon as the symptoms of your headache start, but it may be given at any time during a migraine attack.
- If you did not get any relief after the first dose, do not give a second dose without first talking with your healthcare provider.
- You may use a second dose of Sumavel DosePro or 1 dose of another sumatriptan medicine separated by at least 1 hour, but not sooner, if your headache came back after your first dose.
- Do not use more than 2 doses of 6 mg or 3 doses of 4 mg Sumavel DosePro in a 24-hour period.
- If you use too much Sumavel DosePro, call your healthcare provider or go to the nearest hospital emergency room right away.
- You should write down when you have headaches and when you take Sumavel DosePro so you can talk with your healthcare provider about how Sumavel DosePro is working for you.

What should I avoid while taking Sumavel DosePro?

Sumavel DosePro can cause dizziness, weakness, or drowsiness. If you have these symptoms, do not drive a car, use machinery, or do anything where you need to be alert.

What are the possible side effects of Sumavel DosePro?

Sumavel DosePro may cause serious side effects, including:

- See “What is the most important information I should know about Sumavel DosePro?”
- stroke
- changes in color or sensation in your fingers and toes (Raynaud’s syndrome)
- stomach and intestinal problems (gastrointestinal and colonic ischemic events)
  Symptoms of gastrointestinal and colonic ischemic events include:
  • sudden or severe stomach pain
  • stomach pain after meals
  • weight loss
  • nausea or vomiting
  • constipation or diarrhea
  • bloody diarrhea
  • fever
- problems with blood circulation to your legs and feet (peripheral vascular ischemia)
  Symptoms of peripheral vascular ischemia include:
  • cramping and pain in your legs or hips
  • feeling of heaviness or tightness in your leg muscles
  • burning or aching pain in your feet or toes while resting
  • numbness, tingling, or weakness in your legs
  • cold feeling or color changes in 1 or both legs or feet

- medication overuse headaches. Some people who use too many Sumavel DosePro injections may have worse headaches (medication overuse headache). If your headaches get worse, your healthcare provider may decide to stop your treatment with Sumavel DosePro.
- serotonin syndrome. Serotonin syndrome is a rare but serious problem that can happen in people using Sumavel DosePro, especially if Sumavel DosePro is used with anti-depressant medicines called SSRIs or SNRIs.
  Call your healthcare provider right away if you have any of the following symptoms of serotonin syndrome:
  • mental changes such as seeing things that are not there (hallucinations), agitation, or coma
  • fast heartbeat
  • changes in blood pressure
  • high body temperature
  • tight muscles
  • trouble walking

- seizures. Seizures have happened in people taking Sumavel DosePro who have never had seizures before. Talk with your healthcare provider about your chance of having seizures while you take Sumavel DosePro.

The most common side effects of Sumavel DosePro include:

- pain or redness at your injection site
- tingling or numbness in your fingers or toes
- dizziness
- warm, hot, burning feeling to your face (flushing)
- discomfort or stiffness in your neck
- feeling weak, drowsy, or tired

Tell your healthcare provider if you have any side effect that bothers you or that does not go away.

These are not all the possible side effects of Sumavel DosePro. For more information, ask your healthcare provider or pharmacist.

Call your doctor for medical advice about side effects. You may report side effects to the FDA at 1-800-FDA-1088.

How should I store Sumavel DosePro Injection?

- Store Sumavel DosePro between 68 oF to 77 oF (20 oC to 25 oC).
- Do not freeze.
- Protect from light.

Keep Sumavel DosePro and all medicines out of the reach of children.

General information about the safe and effective use of Sumavel DosePro.

Medicines are sometimes prescribed for purposes other than those listed in Patient Information leaflets. Do not use Sumavel DosePro for a condition for which it was not prescribed. Do not give Sumavel DosePro to other people, even if they have the same symptoms you have. It may harm them.

This Patient Information leaflet summarizes the most important information about Sumavel DosePro. If you would like more information, talk with your healthcare provider. You can ask your healthcare provider or pharmacist for information about Sumavel DosePro that is written for healthcare professionals.

For more information, go to www.SumavelDosePro.com or call 1-866-ZOGENIX

What are the ingredients in Sumavel DosePro Injection?

Active ingredient: sumatriptan succinate

Inactive ingredients: sodium chloride, water for injection

Instructions for Use
Sumavel® DosePro® (SUE-muh-vell DOSE-pro)
(sumatriptan injection)
Needle-free Delivery System

Read these Instructions for Use which come with Sumavel DosePro before you start using it and each time you get a refill. Follow these instructions each time you use Sumavel DosePro. Before you use Sumavel DosePro for the first time, make sure your doctor shows you the right way to use it.

A. Check your device:

The snap-off tip should sit firmly on the end of the clear medication chamber. Do not use Sumavel DosePro if the snap-off tip is tilted or broken off.

The medicine inside Sumavel DosePro should be clear and colorless or pale yellow. Do not use Sumavel DosePro if the medicine looks dark-colored or cloudy.

The expiration date is printed on both the Sumavel DosePro label and carton. Do not use Sumavel DosePro if the medicine is expired.

B. Choose a delivery site:

Select a delivery site such as your stomach area (abdomen) or your thigh.

Do not deliver Sumavel DosePro in the arm.

Your skin should be clean, dry, and free of clothing.

Do not deliver through your clothes.

Do not deliver into scars or moles, or within 2 inches of your belly button (navel). Do not deliver into the same spot. Change delivery sites with each use.

Shaded areas show all possible areas of delivery.

1. Snap: In this step, you will learn how to correctly remove the snap-off tip.

Do not begin these steps until you are ready to take your dose.

Firmly hold the handle of Sumavel DosePro in one hand. With the other hand, use your fingers to grip the top and bottom of the snap-off tip where the finger grips are located.

To break off the snap-off tip, firmly snap it off in a downward motion. You may need to use some force.

You do not need to twist or pull the snap-off tip; doing so will not work.

2. Flip: In this step, you will learn how to prepare Sumavel DosePro for delivery of the medicine.

Firmly press the lavender (4 mg) or green (6 mg) lever all the way down (away from the clear plastic end), until it clicks and locks into the handle. You may feel some resistance – this is normal.

Once you have flipped the lever, do not touch the end of the clear medication chamber. Keep the medication chamber pointed away from your face or eyes.

3. Pinch and Press: In this step, you will learn how to deliver the medicine.

Deliver the dose exactly as shown to you by your healthcare provider.

Pinch about 2 inches of the skin of your stomach (abdomen) or thigh to create a firm section of skin.

Place Sumavel DosePro straight out from the delivery site with the end of the clear medication chamber against your skin.

Do not hold Sumavel DosePro at an angle to your skin.

During the next step, you will hear a loud burst of air. Do not be alarmed – this indicates that the medicine has been delivered.

Steadily press Sumavel DosePro straight down against your skin until you hear and feel a burst of air. There is no button to push. After you hear the burst of air (whoosh), the medicine has been delivered and you can remove Sumavel DosePro from your skin.

Let go of your pinched skin after the medicine has been delivered.

After removing Sumavel DosePro from your skin, a small droplet of blood may be present. You can gently press a cotton ball or gauze over the injection site. Do not rub the injection site. You may cover the injection site with a small adhesive bandage, if needed.

This Patient Information and Instructions for Use has been approved by the U.S. Food and Drug Administration.

Manufactured by Patheon UK, Limited
Swindon, United Kingdom

Manufactured for:
Zogenix, Inc.
San Diego, CA 92130

US Patent Nos. 5,891,086; 5,957,886; 6,135,979; 6,174,304; 6,251,091; 6,280,410; 6,681,810; 7,776,007; 7,901,385; 8,118,771; 8,241,243; 8,241,244; 8,267,903; 8,287,489; 8,343,130; and 8,491,524.

Sumavel® and DosePro® are registered trademarks of Zogenix, Inc.
©2014, Zogenix, Inc. All rights reserved.

PACKAGE LABEL

PRINCIPAL DISPLAY PANEL
NDC 43376-106-01
Sumavel® DosePro
(sumatriptan injection)
Needle-free delivery system
6 mg/0.5 mL
Rx Only

PACKAGE LABEL

PRINCIPAL DISPLAY PANEL
NDC 43376-104-01
Sumavel® DosePro
(sumatriptan injection)
Needle-free delivery system
4 mg/0.5 mL
Rx Only